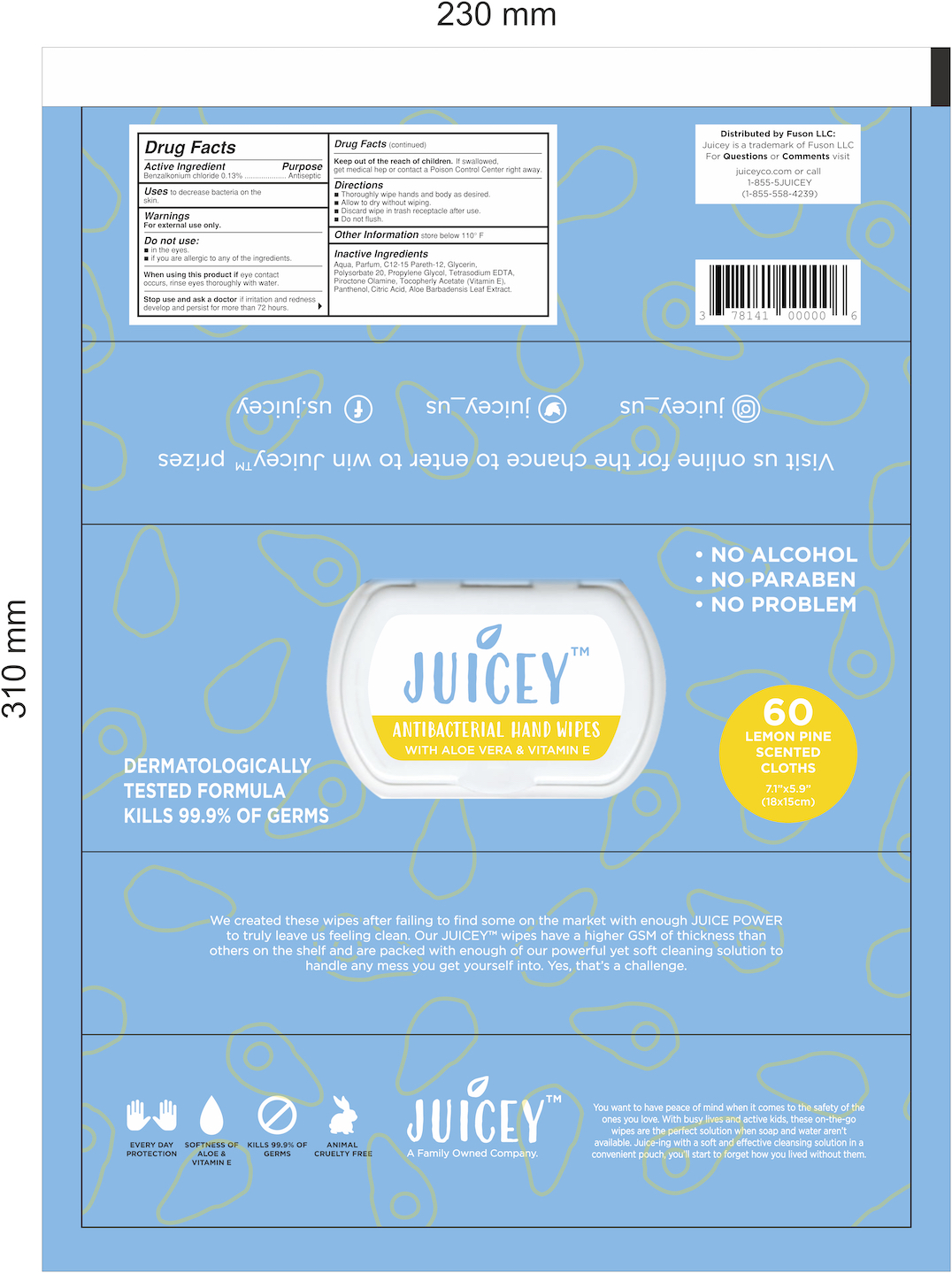 DRUG LABEL: Juicey Antibacterial Wipes
NDC: 80783-901 | Form: CLOTH
Manufacturer: MEHMET YILDIZ YILDIZ KOZMETIK
Category: otc | Type: HUMAN OTC DRUG LABEL
Date: 20201027

ACTIVE INGREDIENTS: BENZALKONIUM CHLORIDE 0.007 g/5.33 g
INACTIVE INGREDIENTS: PROPYLENE GLYCOL; ALOE VERA LEAF; POLYSORBATE 20; .ALPHA.-TOCOPHEROL ACETATE; WATER; C12-15 PARETH-12; GLYCERIN; CITRIC ACID MONOHYDRATE; EDETATE SODIUM; PANTHENOL; PIROCTONE OLAMINE

Juicey Antibacterial Wipes Pouch

Active Ingredient

Benzalkonium Chloride 0.13% v/v - antiseptic

Inactive Ingredients

Aqua, Parfum, C12-15 Pareth-12, Glycerin, Polysorbate 20, Propylene Glycol, Tetrasodium EDTA, Piroctone Olamine, Tocopheryl Acetate (Vitamin E), Panthenol, Citric Acid, Aloebarbadensis Leaf Extract

Purpose

Antiseptic- antibacterial hand towelettes

Use

Wipes used on hands to reduce bacteria on the skin

Warnings

Product contains flammable liquid. Keep away from flame and direct sunlight. Children should not use this product without adult supervision. For external use only. If ingested, call the National Toxication Information Center or seek medical attention. Keep away from eyes.

Do not use if allergic to any of its ingredients. Do not use near eyes. Do not use on children under 2 months of age. Consult a doctor before use if pregnant, breast feeding, have sensitive skin, or are under the age of 12. Do not buy if packaging was opened and/or damaged.

When Using

In case of eye contact, remove any contact lenses and flush eyes repeatedly with water. In case of swallowing, contact a poison control center or seek medical attention.

KEEP OUT OF REACH OF CHILDREN

Store out of reach of children. Children under the age of 12 should be supervised during use.

Directions

Open the hard plastic snap cover to reveal the adhesive label that reads "OPEN". Peel back the adhesive label and remove one wipe at a time. Wipe your hands with the antibacterial wipe until all of the solution is absorbed. Seal the packaging tightly when done.

Storage

Store in a cool, dry place. Store out of reach of children. Do not store near food, drinks, or animal feed. Store away from direct sunlight and open flame.

Package Label

60 Count Antibacterial Wipes Pouch NDC: 80783-901-60